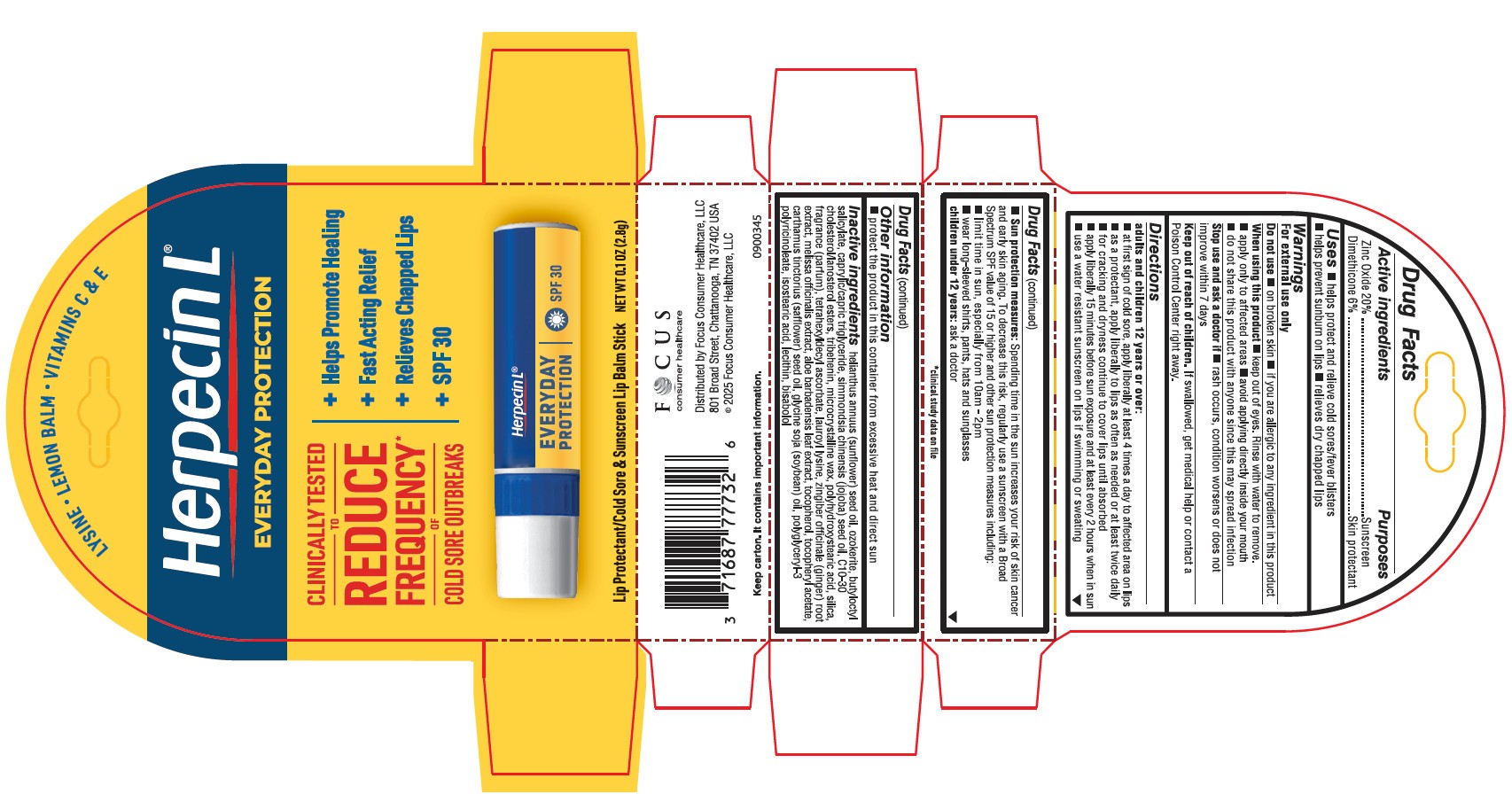 DRUG LABEL: Herpecin L
NDC: 71687-7774 | Form: STICK
Manufacturer: Focus Consumer Healthcare, LLC
Category: otc | Type: HUMAN OTC DRUG LABEL
Date: 20260126

ACTIVE INGREDIENTS: DIMETHICONE 6 g/100 g; ZINC OXIDE 20 g/100 g
INACTIVE INGREDIENTS: SAFFLOWER OIL; SOYBEAN OIL; ISOSTEARIC ACID; POLYHYDROXYSTEARIC ACID (2300 MW); SUNFLOWER OIL; SIMMONDSIA CHINENSIS (JOJOBA) SEED OIL; CERESIN; BUTYLOCTYL SALICYLATE; C10-30 CHOLESTEROL/LANOSTEROL ESTERS; TRIBEHENIN; MICROCRYSTALLINE WAX; SILICON DIOXIDE; LEMON BALM OIL; .ALPHA.-TOCOPHEROL; BISABOLOL; LAUROYL LYSINE; ZINGIBER OFFICINALE (GINGER) ROOT OIL; ALOE BARBADENSIS LEAF JUICE; TETRAHEXYLDECYL ASCORBATE; CAPRYLIC/CAPRIC TRIGLYCERIDE; POLYGLYCERYL-3 RICINOLEATE; ALPHA-TOCOPHEROL ACETATE; LECITHIN, SUNFLOWER

Herpecin L zinc formula

Active ingredients

Zinc Oxide 20%

Dimethicone 6%

Purpose

Sunscreen

Skin protectant

Uses

- helps protect and relieve cold sores/fever blisters
- helps prevent sunburn on lips
- relieves dry chapped lips

Warnings

For external use only

Do not use

- on broken skin
- if you are allergic to any ingredient in this product

When using this product

- keep out of eyes. Rinse with water to remove.
- apply only to affected areas
- avoid applying directly inside your mouth
- do not share this product with anyone since this may spread infection

Stop use and ask a doctor if

- rash occurs, condition worsens or does not improve within 7 days

Keep out of reach of children

If swallowed, get medical help or contact a Poison Control Center right away.

Directions

adults and children 12 years or over:

- at first sign of a cold sore, apply liberally at least 4 times a day to affected area on lips
- as a protectant, aply liberally to lips as often as needed or at least twice daily
- for cracking and dryness continue to cover lips until absorbed
- apply liberally 15 minutes before sun exposure and at least every 2 hours when in sun
- use a water resistant sunscreen on lips if swimming or sweating
- Sun protection measures: Spending time in the sun increases your risk of skin cancer and early skin aging. To decrease this risk, regularily use a sunscreen with a Broad Spectrum SPF value of 15 or higher and other sun protection measures including:
- limit time in sun, especially from 10am - 2pm
- Wear long-sleeved shirts, pants, hats and sunglasses

children under 12 years: ask a doctor

Other information

- protect the product in this container from excessive heat and direct sun

Inactive ingredients

helianthus annuus (sunflower) seed oil, ozokerite, butyloctyl salicylate, caprylic/capric triglyceride, simmondsia chinensis (jojoba) seed oil, C10-30 cholesterol/lanosterol esters, tribehenin, microcrystalline wax, polyhydroxystearic acid, silica, fragrance (parfum), tetrahexyldecyl ascorbate, lauroyl lysine, zingibar officinale (ginger) root extract, melissa officinalis extract, aloe barbadensis leaf extract, tocopherol, tocopheryl acetate, carthamus tinctorius (safflower) seed oil, glycine soja (soybean) oil, polyglyceryl-3 polyricinoleate, isostearic acid, lecithin, bisabolol